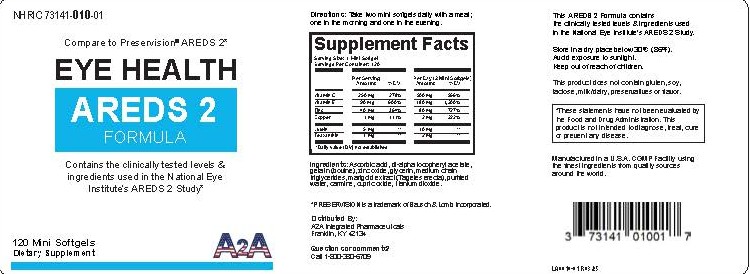 DRUG LABEL: EYE HEALTH AREDS 2 FORMULA
NDC: 73141-010 | Form: CAPSULE, GELATIN COATED
Manufacturer: A2A INTEGRATED PHARMACEUTICALS, LLC
Category: other | Type: DIETARY SUPPLEMENT
Date: 20250331

ACTIVE INGREDIENTS: ZINC OXIDE 40 mg/1 1; ASCORBIC ACID 250 mg/1 1; CUPRIC OXIDE 1 mg/1 1; VITAMIN E POLYETHYLENE GLYCOL SUCCINATE 90 mg/1 1
INACTIVE INGREDIENTS: ZEAXANTHIN 1 mg/1 1; LUTEIN 5 mg/1 1; GLYCERIN; TAGETES ERECTA WHOLE; WATER; GELATIN TYPE B BOVINE (200 BLOOM); MEDIUM-CHAIN TRIGLYCERIDES; TITANIUM DIOXIDE; CARMINIC ACID

EYE HEALTH AREDS 2 FORMULA

Supplement Facts

Serving Size: 1 Mini Softgel

Servings Per Container: 120

 | Per Serving Amount | %DV | Per Day Amount (2 Mini Softgels) | %DV
Vitamin C | 250 mg | 278% | 500 mg | 556%
Vitamin E | 90 mg | 600% | 180 mg | 1200%
Zinc | 40 mg | 364% | 80 mg | 727%
Copper | 1 mg | 111% | 2 mg | 222%
Lutein | 5 mg | ** | 10 mg | **
Zeaxanthin | 1 mg | ** | 2 mg | **
**Daily Value (DV) not established

Ingredients: Ascorbic acid, dl-alpha tocopheryl acetate, gelatin (bovine), zinc oxide, glycerin, medium

chain triglycerides, marigold extract (Tagetes erecta), purified water, carmine, cupric oxide, titatnium dioxide.

*PRESERVISION is a trademark of Bausch & Lomb Incorporated.

Distributed By:

A2A Integrated Pharmaceuticals

Franklin KY, 42134

Questions or comments?

Call 1-800-380-6709

Directions

Take two mini softgels daily with a meal; one in the morning and one in the evening.

Health Claim

^These statements have not been evaluated by the Food and Drug Administration. This product is not intended to diagnose, treat, cure or prevent any disease.

SAFE HANDLING WARNING

This AREDS 2 Formula contains the clinically tested levels & ingredients used in the National Eye Institute's AREDS 2 Study.

Store in a dry place below 30°C (86°F).

Avoid exposure to sunlight.

Keep out of reach of children.

This product does not contain gluten, soy, lactose, milk/dairy, preservatives or flavor.

Manufactured in a U.S.A. CGMP Facility using the finest ingredients from quality sources around the world.

Principal Display Panel

NHRIC 73141-010-01

Compare to Preservision® AREDS 2*

EYE HEALTH

AREDS 2

FORMULA

Contains the clinically tested levels &

ingredients used in the National Eye

Institute's AREDS 2 Study^

120 Mini Softgels

Dietary Supplement